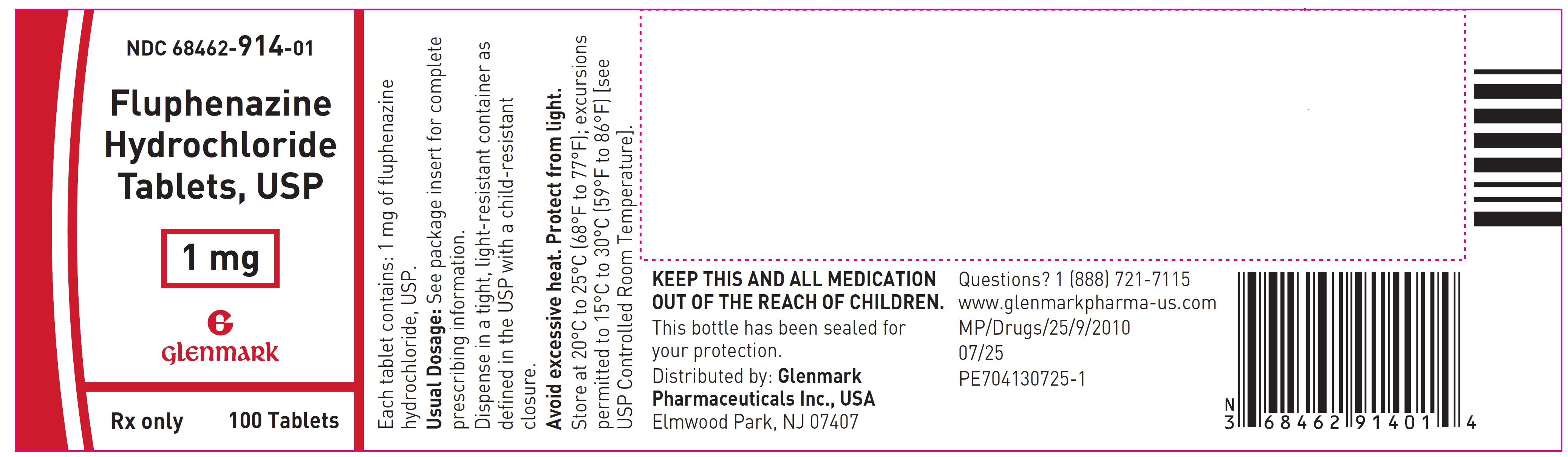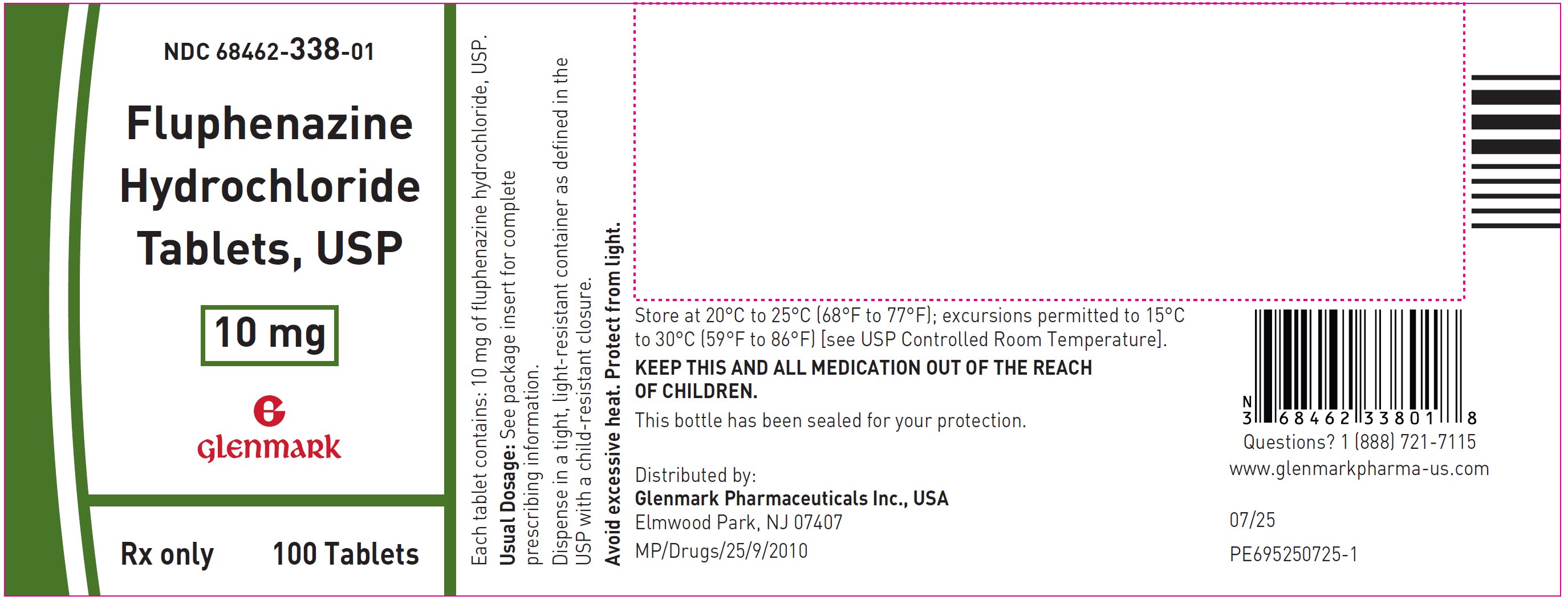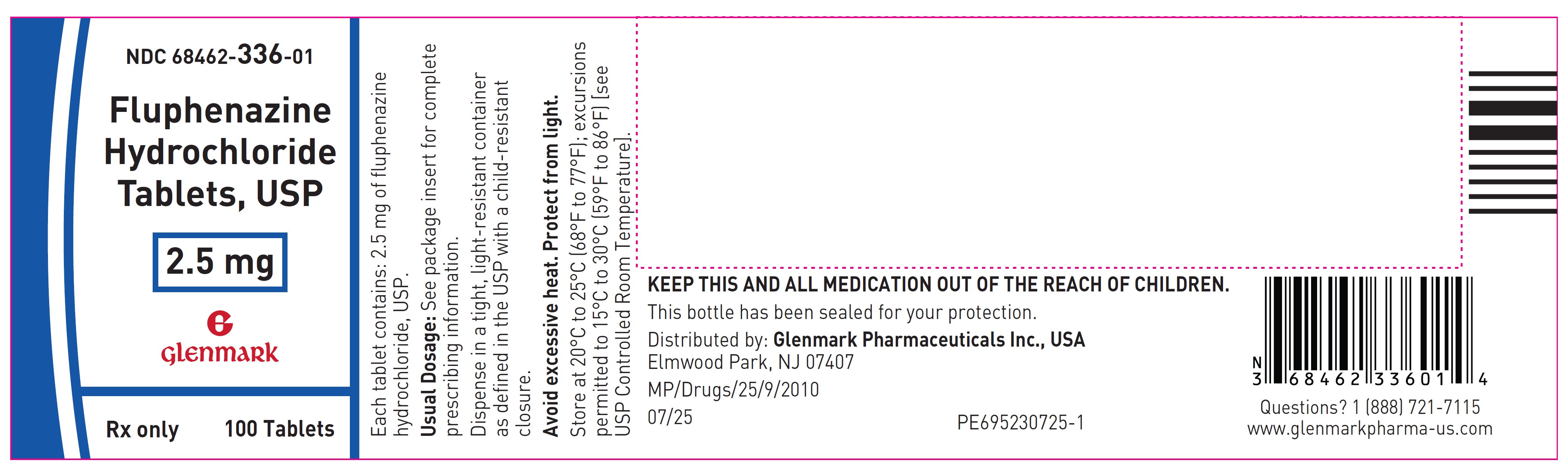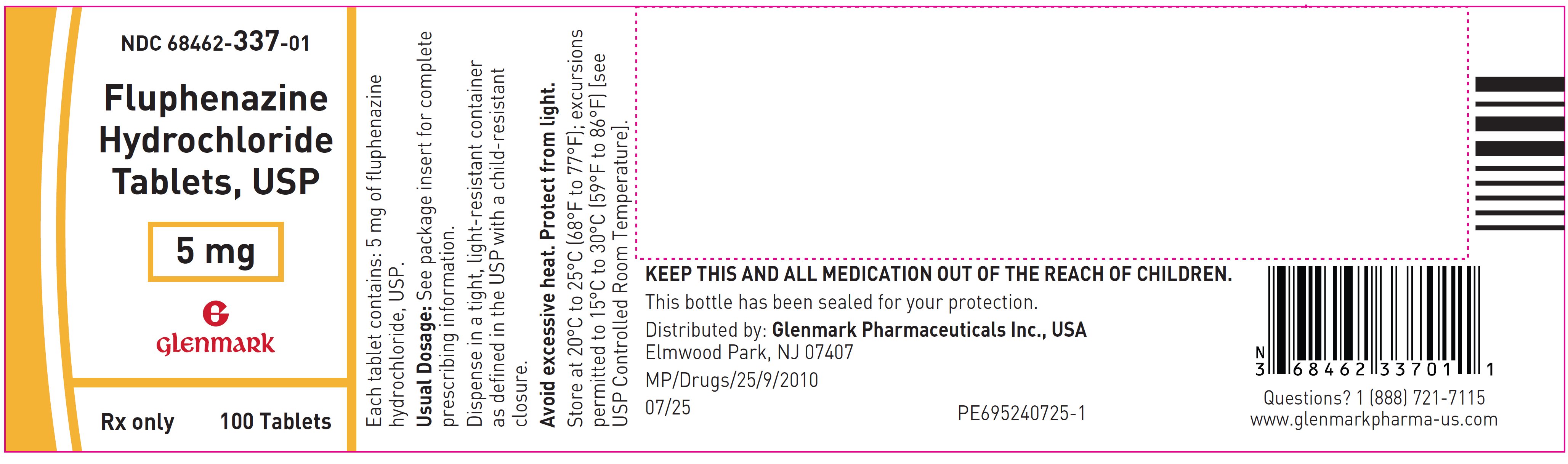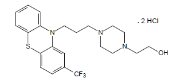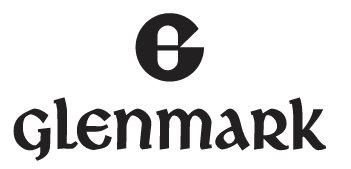 DRUG LABEL: Fluphenazine Hydrochloride
NDC: 68462-914 | Form: TABLET, FILM COATED
Manufacturer: Glenmark Pharmaceuticals Inc., USA
Category: prescription | Type: HUMAN PRESCRIPTION DRUG LABEL
Date: 20260129

ACTIVE INGREDIENTS: FLUPHENAZINE HYDROCHLORIDE 1 mg/1 1
INACTIVE INGREDIENTS: LACTOSE MONOHYDRATE; MICROCRYSTALLINE CELLULOSE; CROSCARMELLOSE SODIUM; STARCH, CORN; SILICON DIOXIDE; MAGNESIUM STEARATE; HYPROMELLOSE, UNSPECIFIED; TITANIUM DIOXIDE; POLYETHYLENE GLYCOL, UNSPECIFIED; FD&C BLUE NO. 2; D&C YELLOW NO. 10; FD&C YELLOW NO. 6; WATER

Fluphenazine Hydrochloride Tablets, USP

Rx only

WARNING

Increased Mortality in Elderly Patients with Dementia-Related Psychosis:

Elderly patients with dementia-related psychosis treated with antipsychotic drugs are at an increased risk of death. Analyses of seventeen placebo-controlled trials (modal duration of 10 weeks), largely in patients taking atypical antipsychotic drugs, revealed a risk of death in drug-treated patients of between 1.6 to 1.7 times the risk of death in placebo-treated patients. Over the course of a typical 10-week controlled trial, the rate of death in drug-treated patients was about 4.5%, compared to a rate of about 2.6% in the placebo group. Although the causes of death were varied, most of the deaths appeared to be either cardiovascular (e.g., heart failure, sudden death) or infectious (e.g., pneumonia) in nature. Observational studies suggest that, similar to atypical antipsychotic drugs, treatment with conventional antipsychotic drugs may increase mortality. The extent to which the findings of increased mortality in observational studies may be attributed to the antipsychotic drug as opposed to some characteristic(s) of the patients is not clear. Fluphenazine hydrochloride is not approved for the treatment of patients with dementia-related psychosis (see WARNINGS).

DESCRIPTION

Fluphenazine hydrochloride, USP is a trifluoromethyl phenothiazine derivative intended for the management of schizophrenia. The chemical designation is 4-[3-[2-(trifluoromethyl) phenothiazin-10-yl] propyl]-1-piperazine-ethanol dihydrochloride.

The structural formula is represented below:

Molecular Formula: C22H26F3N3OS·2HCl Molecular Weight: 510.44

Fluphenazine Hydrochloride Tablets, USP, for oral administration, contain 1 mg, 2.5 mg, 5 mg, or 10 mg fluphenazine hydrochloride, USP per tablet. Each tablet also contains colloidal silicon dioxide, croscarmellose sodium, D&C Red No. 27 (2.5 mg tablet), D&C Yellow No. 10 (1 mg and 5 mg tablet), FD&C Blue No. 2 (1 mg, 2.5 mg and 5 mg tablet), FD&C Red No. 40 (10 mg tablet), FD&C Yellow No. 6 (1 mg, 5 mg and 10 mg tablet), hypromellose, lactose monohydrate, magnesium stearate, microcrystalline cellulose, polyethylene glycol, pregelatinized starch, purified water, and titanium dioxide.

CLINICAL PHARMACOLOGY

Fluphenazine hydrochloride has activity at all levels of the central nervous system as well as on multiple organ systems. The mechanism whereby its therapeutic action is exerted is unknown.

INDICATIONS AND USAGE

Fluphenazine hydrochloride tablets are indicated in the management of manifestations of psychotic disorders.

Fluphenazine hydrochloride has not been shown effective in the management of behavioral complications in patients with mental retardation.

CONTRAINDICATIONS

Phenothiazines are contraindicated in patients with suspected or established subcortical brain damage, in patients receiving large doses of hypnotics, and in comatose or severely depressed states. The presence of blood dyscrasia or liver damage precludes the use of fluphenazine hydrochloride. Fluphenazine hydrochloride is contraindicated in patients who have shown hypersensitivity to fluphenazine; cross-sensitivity to phenothiazine derivatives may occur.

WARNINGS

Increased Mortality in Elderly Patients with Dementia-Related Psychosis:

Elderly patients with dementia-related psychosis treated with antipsychotic drugs are at an increased risk of death. Fluphenazine hydrochloride is not approved for the treatment of patients with dementia-related psychosis (see BOXED WARNING).

Tardive Dyskinesia:

Tardive dyskinesia, a syndrome consisting of potentially irreversible, involuntary, dyskinetic movements may develop in patients treated with neuroleptic (antipsychotic) drugs. Although the prevalence of the syndrome appears to be highest among the elderly, especially elderly women, it is impossible to rely upon prevalence estimates to predict, at the inception of neuroleptic treatment, which patients are likely to develop the syndrome. Whether neuroleptic drug products differ in their potential to cause tardive dyskinesia is unknown.

Both the risk of developing the syndrome and the likelihood that it will become irreversible are believed to increase as the duration of treatment and the total cumulative dose of neuroleptic drugs administered to the patient increase. However, the syndrome can develop, although much less commonly, after relatively brief treatment periods at low doses.

There is no known treatment for established cases of tardive dyskinesia, although the syndrome may remit, partially or completely, if neuroleptic treatment is withdrawn. Neuroleptic treatment itself, however, may suppress (or partially suppress) the signs and symptoms of the syndrome and thereby may possibly mask the underlying disease process. The effect that symptomatic suppression has upon the long-term course of the syndrome is unknown.

Given these considerations, neuroleptics should be prescribed in a manner that is most likely to minimize the occurrence of tardive dyskinesia. Chronic neuroleptic treatment should generally be reserved for patients who suffer from a chronic illness that, 1) is known to respond to neuroleptic drugs, and, 2) for whom alternative, equally effective, but potentially less harmful treatments are not available or appropriate. In patients who do require chronic treatment, the smallest dose and the shortest duration of treatment producing a satisfactory clinical response should be sought. The need for continued treatment should be reassessed periodically.

If signs and symptoms of tardive dyskinesia appear in a patient on neuroleptics, drug discontinuation should be considered. However, some patients may require treatment despite the presence of the syndrome.

(For further information about the description of tardive dyskinesia and its clinical detection, please refer to the sections on PRECAUTIONS, Information for Patients and ADVERSE REACTIONS, Tardive Dyskinesia.)

Neuroleptic Malignant Syndrome (NMS):

A potentially fatal symptom complex sometimes referred to as Neuroleptic Malignant Syndrome (NMS) has been reported in association with antipsychotic drugs. Clinical manifestations of NMS are hyperpyrexia, muscle rigidity, altered mental status and evidence of autonomic instability (irregular pulse or blood pressure, tachycardia, diaphoresis, and cardiac dysrhythmias).

The diagnostic evaluation of patients with this syndrome is complicated. In arriving at a diagnosis, it is important to identify cases where the clinical presentation includes both serious medical illness (e.g., pneumonia, systemic infection, etc.) and untreated or inadequately treated extrapyramidal signs and symptoms (EPS). Other important considerations in the differential diagnosis include central anticholinergic toxicity, heat stroke, drug fever and primary central nervous system (CNS) pathology.

The management of NMS should include: 1) immediate discontinuation of antipsychotic drugs and other drugs not essential to concurrent therapy, 2) intensive symptomatic treatment and medical monitoring, and, 3) treatment of any concomitant serious medical problems for which specific treatments are available. There is no general agreement about specific pharmacological treatment regimens for uncomplicated NMS.

If a patient requires antipsychotic drug treatment after recovery from NMS, the potential reintroduction of drug therapy should be carefully considered. The patient should be carefully monitored, since recurrences of NMS have been reported.

The use of this drug may impair the mental and physical abilities required for driving a car or operating heavy machinery.

Potentiation of the effects of alcohol may occur with the use of this drug.

Since there is no adequate experience in children who have received this drug, safety and efficacy in children have not been established.

Falls

Fluphenazine hydrochloride tablets may cause somnolence, postural hypotension, motor and sensory instability, which may lead to falls and, consequently, fractures or other injuries. For patients with diseases, conditions, or medications that could exacerbate these effects, complete fall risk assessments when initiating antipsychotic treatment and recurrently for patients on long-term antipsychotic therapy.

Usage in Pregnancy:

The safety for the use of this drug during pregnancy has not been established; therefore, the possible hazards should be weighed against the potential benefits when administering this drug to pregnant patients.

Non-teratogenic Effects

Neonates exposed to antipsychotic drugs, during the third trimester of pregnancy are at risk for extrapyramidal and/or withdrawal symptoms following delivery. There have been reports of agitation, hypertonia, hypotonia, tremor, somnolence, respiratory distress and feeding disorder in these neonates. These complications have varied in severity; while in some cases symptoms have been self-limited, in other cases neonates have required intensive care unit support and prolonged hospitalization.

Fluphenazine hydrochloride should be used during pregnancy only if the potential benefit justifies the potential risk to the fetus.

PRECAUTIONS

General:

Because of the possibility of cross-sensitivity, fluphenazine hydrochloride should be used cautiously in patients who have developed cholestatic jaundice, dermatoses or other allergic reactions to phenothiazine derivatives.

Psychotic patients on large doses of a phenothiazine drug who are undergoing surgery should be watched carefully for possible hypotensive phenomena. Moreover, it should be remembered that reduced amounts of anesthetics or central nervous system depressants may be necessary.

The effects of atropine may be potentiated in some patients receiving fluphenazine hydrochloride because of added anticholinergic effects.

Fluphenazine hydrochloride should be used cautiously in patients exposed to extreme heat or phosphorus insecticides; in patients with a history of convulsive disorders, since grand mal convulsions have been known to occur; and in patients with special medical disorders, such as mitral insufficiency or other cardiovascular diseases and pheochromocytoma.

The possibility of liver damage, pigmentary retinopathy, lenticular and corneal deposits, and development of irreversible dyskinesia should be remembered when patients are on prolonged therapy.

Neuroleptic drugs elevate prolactin levels; the elevation persists during chronic administration. Tissue culture experiments indicate that approximately one-third of human breast cancers are prolactin dependent in vitro, a factor of potential importance if the prescription of these drugs is contemplated in a patient with a previously detected breast cancer. Although disturbances such as galactorrhea, amenorrhea, gynecomastia, and impotence have been reported, the clinical significance of elevated serum prolactin levels is unknown for most patients. An increase in mammary neoplasms has been found in rodents after chronic administration of antipsychotic drugs. Published epidemiologic studies have shown inconsistent results when exploring the association between hyperprolactinemia and breast cancer.

Information for Patients:

Given the likelihood that some patients exposed chronically to neuroleptics will develop tardive dyskinesia, it is advised that all patients in whom chronic use is contemplated be given, if possible, full information about this risk. The decision to inform patients and/or their guardians must obviously take into account the clinical circumstances and the competency of the patient to understand the information provided.

Abrupt Withdrawal:

In general, phenothiazines do not produce psychic dependence; however, gastritis, nausea and vomiting, dizziness, and tremulousness have been reported following abrupt cessation of high dose therapy. Reports suggest that these symptoms can be reduced if concomitant antiparkinsonian agents are continued for several weeks after the phenothiazine is withdrawn.

Facilities should be available for periodic checking of hepatic function, renal function and the blood picture. Renal function of patients on long-term therapy should be monitored; if BUN (blood urea nitrogen) becomes abnormal, treatment should be discontinued.

As with any phenothiazine, the physician should be alert to the possible development of “silent pneumonias” in patients under treatment with fluphenazine hydrochloride.

Leukopenia, Neutropenia and Agranulocytosis:

In clinical trial and postmarketing experience, events of leukopenia/neutropenia have been reported temporally related to antipsychotic agents, including fluphenazine hydrochloride USP. Agranulocytosis (including fatal cases) has also been reported. Possible risk factors for leukopenia/neutropenia include preexisting low white blood cell count (WBC) and history of drug induced leukopenia/neutropenia. Patients with a preexisting low WBC or a history of drug induced leukopenia/neutropenia should have their complete blood count (CBC) monitored frequently during the first few months of therapy and should discontinue fluphenazine hydrochloride USP at the first sign of a decline in WBC in the absence of other causative factors.

Patients with neutropenia should be carefully monitored for fever or other symptoms or signs of infection and treated promptly if such symptoms or signs occur. Patients with severe neutropenia (absolute neutrophil count <1000/mm^3) should discontinue fluphenazine hydrochloride USP and have their WBC followed until recovery.

ADVERSE REACTIONS

Central Nervous System:

The side effects most frequently reported with phenothiazine compounds are extrapyramidal symptoms including pseudoparkinsonism, dystonia, dyskinesia, akathisia, oculogyric crises, opisthotonos, and hyperreflexia. Most often these extrapyramidal symptoms are reversible; however, they may be persistent (see BELOW). With any given phenothiazine derivative, the incidence and severity of such reactions depend more on individual patient sensitivity than on other factors, but dosage level and patient age are also determinants.

Extrapyramidal reactions may be alarming, and the patient should be forewarned and reassured. These reactions can usually be controlled by administration of antiparkinsonian drugs such as benztropine mesylate or intravenous caffeine and sodium benzoate injection, and by subsequent reduction in dosage.

Extrapyramidal Symptoms:

Dystonia: Class Effect: Symptoms of dystonia, prolonged abnormal contractions of muscle groups, may occur in susceptible individuals during the first few days of treatment. Dystonic symptoms include: spasm of the neck muscles, sometimes progressing to tightness of the throat, swallowing difficulty, difficulty breathing, and/or protrusion of the tongue. While these symptoms can occur at low doses, they occur more frequently and with greater severity with high potency and at higher doses of first generation antipsychotic drugs. An elevated risk of acute dystonia is observed in males and younger age groups.

Tardive Dyskinesia:

See WARNINGS. The syndrome is characterized by involuntary choreoathetoid movements which variously involve the tongue, face, mouth, lips, or jaw (e.g., protrusion of the tongue, puffing of cheeks, puckering of the mouth, chewing movements), trunk and extremities. The severity of the syndrome and the degree of impairment produced vary widely.

The syndrome may become clinically recognizable either during treatment, upon dosage reduction, or upon withdrawal of treatment. Early detection of tardive dyskinesia is important. To increase the likelihood of detecting the syndrome at the earliest possible time, the dosage of neuroleptic drug should be reduced periodically (if clinically possible) and the patient observed for signs of the disorder. This maneuver is critical, since neuroleptic drugs may mask the signs of the syndrome.

Other CNS Effects:

Occurrences of neuroleptic malignant syndrome (NMS) have been reported in patients on neuroleptic therapy (see WARNINGS, Neuroleptic Malignant Syndrome); leukocytosis, elevated CPK, liver function abnormalities, and acute renal failure may also occur with NMS.

Drowsiness or lethargy, if they occur, may necessitate a reduction in dosage; the induction of a catatonic-like state has been known to occur with dosages of fluphenazine far in excess of the recommended amounts. As with other phenothiazine compounds, reactivation or aggravation of psychotic processes may be encountered.

Phenothiazine derivatives have been known to cause, in some patients, restlessness, excitement, or bizarre dreams.

Autonomic Nervous System:

Hypertension and fluctuations in blood pressure have been reported with fluphenazine hydrochloride.

Hypotension has rarely presented a problem with fluphenazine. However, patients with pheochromocytoma, cerebral vascular or renal insufficiency, or a severe cardiac reserve deficiency such as mitral insufficiency appear to be particularly prone to hypotensive reactions with phenothiazine compounds, and should therefore be observed closely when the drug is administered.

If severe hypotension should occur, supportive measures including the use of intravenous vasopressor drugs should be instituted immediately. Norepinephrine Bitartrate Injection is the most suitable drug for this purpose; epinephrine should not be used since phenothiazine derivatives have been found to reverse its action, resulting in a further lowering of blood pressure.

Autonomic reactions including nausea and loss of appetite, salivation, polyuria, perspiration, dry mouth, headache, and constipation may occur. Autonomic effects can usually be controlled by reducing or temporarily discontinuing dosage.

In some patients, phenothiazine derivatives have caused blurred vision, glaucoma, bladder paralysis, fecal impaction, paralytic ileus, tachycardia, or nasal congestion.

Metabolic and Endocrine:

Weight change, peripheral edema, abnormal lactation, gynecomastia, menstrual irregularities, false results on pregnancy tests, impotency in men and increased libido in women have all been known to occur in some patients on phenothiazine therapy.

Allergic Reactions:

Skin disorders such as itching, erythema, urticaria, seborrhea, photosensitivity, eczema and even exfoliative dermatitis have been reported with phenothiazine derivatives. The possibility of anaphylactoid reactions occurring in some patients should be borne in mind.

Hematologic:

Routine blood counts are advisable during therapy since blood dyscrasias including leukopenia, agranulocytosis, thrombocytopenic or nonthrombocytopenic purpura, eosinophilia, and pancytopenia have been observed with phenothiazine derivatives. Furthermore, if any soreness of the mouth, gums, or throat, or any symptoms of upper respiratory infection occur and confirmatory leukocyte count indicates cellular depression, therapy should be discontinued and other appropriate measures instituted immediately.

Hepatic:

Liver damage as manifested by cholestatic jaundice may be encountered, particularly during the first months of therapy; treatment should be discontinued if this occurs. An increase in cephalin flocculation, sometimes accompanied by alterations in other liver function tests, has been reported in patients receiving fluphenazine hydrochloride who have had no clinical evidence of liver damage.

Others:

Sudden, unexpected and unexplained deaths have been reported in hospitalized psychotic patients receiving phenothiazines. Previous brain damage or seizures may be predisposing factors; high doses should be avoided in known seizure patients. Several patients have shown sudden flare-ups of psychotic behavior patterns shortly before death. Autopsy findings have usually revealed acute fulminating pneumonia or pneumonitis, aspiration of gastric contents, or intramyocardial lesions.

Although this is not a general feature of fluphenazine, potentiation of central nervous system depressants (opiates, analgesics, antihistamines, barbiturates, alcohol) may occur.

The following adverse reactions have also occurred with phenothiazine derivatives: systemic lupus erythematosus-like syndrome, hypotension severe enough to cause fatal cardiac arrest, altered electrocardiographic and electroencephalographic tracings, altered cerebrospinal fluid proteins, cerebral edema, asthma, laryngeal edema, and angioneurotic edema; with long-term use-skin pigmentation, and lenticular and corneal opacities.

To report SUSPECTED ADVERSE REACTIONS, contact Glenmark Pharmaceuticals Inc., USA at 1 (888) 721-7115 or FDA at 1-800-FDA-1088 or www.fda.gov/medwatch.

DOSAGE AND ADMINISTRATION

Depending on severity and duration of symptoms, total daily dosage for adult psychotic patients may range initially from 2.5 mg to 10 mg and should be divided and given at 6 to 8 hour intervals.

The smallest amount that will produce the desired results must be carefully determined for each individual, since optimal dosage levels of this potent drug vary from patient to patient. In general, the oral dose has been found to be approximately 2 to 3 times the parenteral dose of fluphenazine. Treatment is best instituted with a low initial dosage, which may be increased, if necessary, until the desired clinical effects are achieved. Therapeutic effect is often achieved with doses under 20 mg daily. Patients remaining severely disturbed or inadequately controlled may require upward titration of dosage. Daily doses up to 40 mg may be necessary; controlled clinical studies have not been performed to demonstrate safety of prolonged administration of such doses.

When symptoms are controlled, dosage can generally be reduced gradually to daily maintenance doses of 1 mg to 5 mg, often given as a single daily dose. Continued treatment is needed to achieve maximum therapeutic benefits; further adjustments in dosage may be necessary during the course of therapy to meet the patient’s requirements.

For psychotic patients who have been stabilized on a fixed daily dosage of orally administered fluphenazine hydrochloride dosage forms, conversion to the long-acting fluphenazine decanoate may be indicated (see package insert for fluphenazine decanoate for conversion information).

For geriatric patients, the suggested starting dose is 1 mg to 2.5 mg daily, adjusted according to the response of the patient.

HOW SUPPLIED

Fluphenazine Hydrochloride Tablets, USP are available in four strengths as 1 mg, 2.5 mg, 5 mg or 10 mg of fluphenazine hydrochloride, USP.

The 1 mg tablets are green, round, film-coated tablets debossed with “G 14” on one side and plain on the other side. They are available as follows:

Bottles of 100 with child-resistant closure, NDC 68462-914-01

Bottles of 500 with child-resistant closure, NDC 68462-914-05

Carton of 100 Tablets (10 x 10 unit-dose blister pack), NDC 68462-914-14

The 2.5 mg tablets are blue, round, film-coated tablets debossed with “G 47” on one side and plain on the other side. They are available as follows:

Bottles of 100 with child-resistant closure, NDC 68462-336-01

Bottles of 500 with child-resistant closure, NDC 68462-336-05

Carton of 100 Tablets (10 x 10 unit-dose blister pack), NDC 68462-336-14

The 5 mg tablets are green, round, film-coated tablets debossed with “G 74” on one side and plain on the other side. They are available as follows:

Bottles of 100 with child-resistant closure, NDC 68462-337-01

Bottles of 500 with child-resistant closure, NDC 68462-337-05

Carton of 100 Tablets (10 x 10 unit-dose blister pack), NDC 68462-337-14

The 10 mg tablets are orange to reddish orange, round, film-coated tablets debossed with “G 187” on one side and plain on the other side. They are available as follows:

Bottles of 100 with child-resistant closure, NDC 68462-338-01

Bottles of 500 with child-resistant closure, NDC 68462-338-05

Carton of 100 Tablets (10 x 10 unit-dose blister pack), NDC 68462-338-14

Store at 20°C to 25°C (68°F to 77°F); excursions permitted to 15°C to 30°C (59°F to 86°F) [see USP Controlled Room Temperature]. Avoid excessive heat. Protect from light.

Bottle

Dispense in a tight, light-resistant container as defined in the USP with a child-resistant closure.

Blister

FOR YOUR PROTECTION: Do not use if blister is torn or broken.

Distributed by:

Glenmark Pharmaceuticals Inc., USA

Elmwood Park, NJ 07407

Questions? 1 (888) 721-7115

www.glenmarkpharma-us.com

July 2025